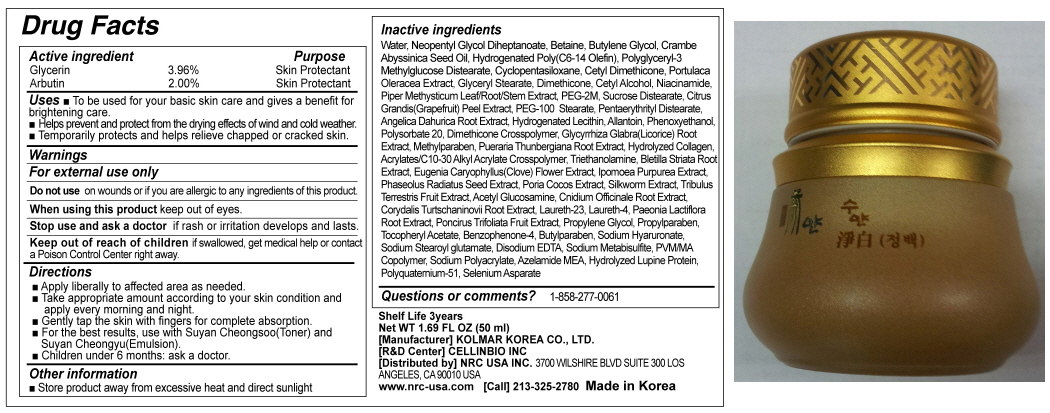 DRUG LABEL: SUYAN JEONGBAEK
NDC: 76173-1007 | Form: CREAM
Manufacturer: Cellinbio Co Ltd
Category: otc | Type: HUMAN OTC DRUG LABEL
Date: 20111109

ACTIVE INGREDIENTS: GLYCERIN 4.8 mL/50 mL; ARBUTIN 1 mL/50 mL
INACTIVE INGREDIENTS: WATER; NEOPENTYL GLYCOL DIHEPTANOATE; BETAINE; BUTYLENE GLYCOL; CRAMBE HISPANICA SUBSP. ABYSSINICA SEED OIL; CYCLOMETHICONE 5; PORTULACA OLERACEA WHOLE; GLYCERYL MONOSTEARATE; DIMETHICONE; CETYL ALCOHOL; NIACINAMIDE; PIPER METHYSTICUM WHOLE; POLYETHYLENE GLYCOL 2000; SUCROSE DISTEARATE; CITRUS MAXIMA FRUIT RIND; PEG-100 STEARATE; PENTAERYTHRITYL DISTEARATE; ANGELICA DAHURICA ROOT; HYDROGENATED SOYBEAN LECITHIN; ALLANTOIN; PHENOXYETHANOL; POLYSORBATE 20; GLYCYRRHIZA GLABRA; METHYLPARABEN; PUERARIA MONTANA VAR. LOBATA ROOT; CARBOMER INTERPOLYMER TYPE A (55000 MPA.S); TROLAMINE; BLETILLA STRIATA BULB; CLOVE; IPOMOEA PURPUREA TOP; MUNG BEAN; FU LING; TRIBULUS TERRESTRIS FRUIT; N-ACETYLGLUCOSAMINE; CNIDIUM OFFICINALE ROOT; CORYDALIS YANHUSUO TUBER; LAURETH-23; LAURETH-4; PAEONIA LACTIFLORA ROOT; PONCIRUS TRIFOLIATA FRUIT; PROPYLENE GLYCOL; PROPYLPARABEN; .ALPHA.-TOCOPHEROL ACETATE, DL-; SULISOBENZONE; BUTYLPARABEN; HYALURONATE SODIUM; DISODIUM STEAROYL GLUTAMATE; EDETATE DISODIUM; SODIUM METABISULFITE; MALEIC ANHYDRIDE; SODIUM POLYACRYLATE (2500000 MW)

SUYAN JEONGBAEK

Drug Facts

Active Ingrdient
Glycerin 3.96%
Arbutin 2.00%

Purpose

Skin Protectant

Keep out of Reach of Children

If swallowed, get medical help or contact a Posion Control Center right away.

Indication & Usage

Directions
■ Apply liberally to affected area as needed.
■ Take appropriate amount according to your skin condition and apply every morning and night.
■ Gently tap the skin with fingers for complete absorption.
■ For the best results, use with Suyan Cheongsoo(Toner) and Suyan Cheongyu(Emulsion).
■ Children under 6 months: ask a doctor.

Warnings

For external use only
Do not use on wounds or if you are allergic to any ingredients of this product.
When using this product keep out of eyes.
Stop use and ask a doctor if rash or irritation develops and lasts.

Dosage & Administration

■ To be used for your basic skin care and gives a benefit for brightening care.
■ Helps prevent and protect from the drying effects of wind and cold weather.
■ Temporarily protects and helps relieve chapped or cracked skin.

Inactive Ingredient

Water, Neopentyl Glycol Diheptanoate, Betaine, Butylene Glycol, Crambe Abyssinica Seed Oil, Hydrogenated Poly(C6-14 Olefin), Polyglyceryl-3 Methylglucose Distearate, Cyclopentasiloxane, Cetyl Dimethicone, Portulaca Oleracea Extract, Glyceryl Stearate, Dimethicone, Cetyl Alcohol, Niacinamide, Piper Methysticum Leaf/Root/Stem Extract, PEG-2M, Sucrose Distearate, Citrus Grandis(Grapefruit) Peel Extract, PEG-100 Stearate, Pentaerythrityl Distearate, Angelica Dahurica Root Extract, Hydrogenated Lecithin, Allantoin, Phenoxyethanol, Polysorbate 20, Dimethicone Crosspolymer, Glycyrrhiza Glabra(Licorice) Root Extract, Methylparaben, Pueraria Thunbergiana Root Extract, Hydrolyzed Collagen, Acrylates/C10-30 Alkyl Acrylate Crosspolymer, Triethanolamine, Bletilla Striata Root Extract, Eugenia Caryophyllus(Clove) Flower Extract, Ipomoea Purpurea Extract, Phaseolus Radiatus Seed Extract, Poria Cocos Extract, Silkworm Extract, Tribulus Terrestris Fruit Extract, Acetyl Glucosamine, Cnidium Officinale Root Extract, Corydalis Turtschaninovii Root Extract, Laureth-23, Laureth-4, Paeonia Lactiflora Root Extract, Poncirus Trifoliata Fruit Extract, Propylene Glycol, Propylparaben, Tocopheryl Acetate, Benzophenone-4, Butylparaben, Sodium Hyaruronate, Sodium Stearoyl glutamate, Disodium EDTA, Sodium Metabisulfite, PVM/MA Copolymer, Sodium Polyacrylate, Azelamide MEA, Hydrolyzed Lupine Protein, Polyquaternium-51, Selenium Asparate

SUYAN JEONGBAEK

Net WT. 1.69 FL OZ(50ml)